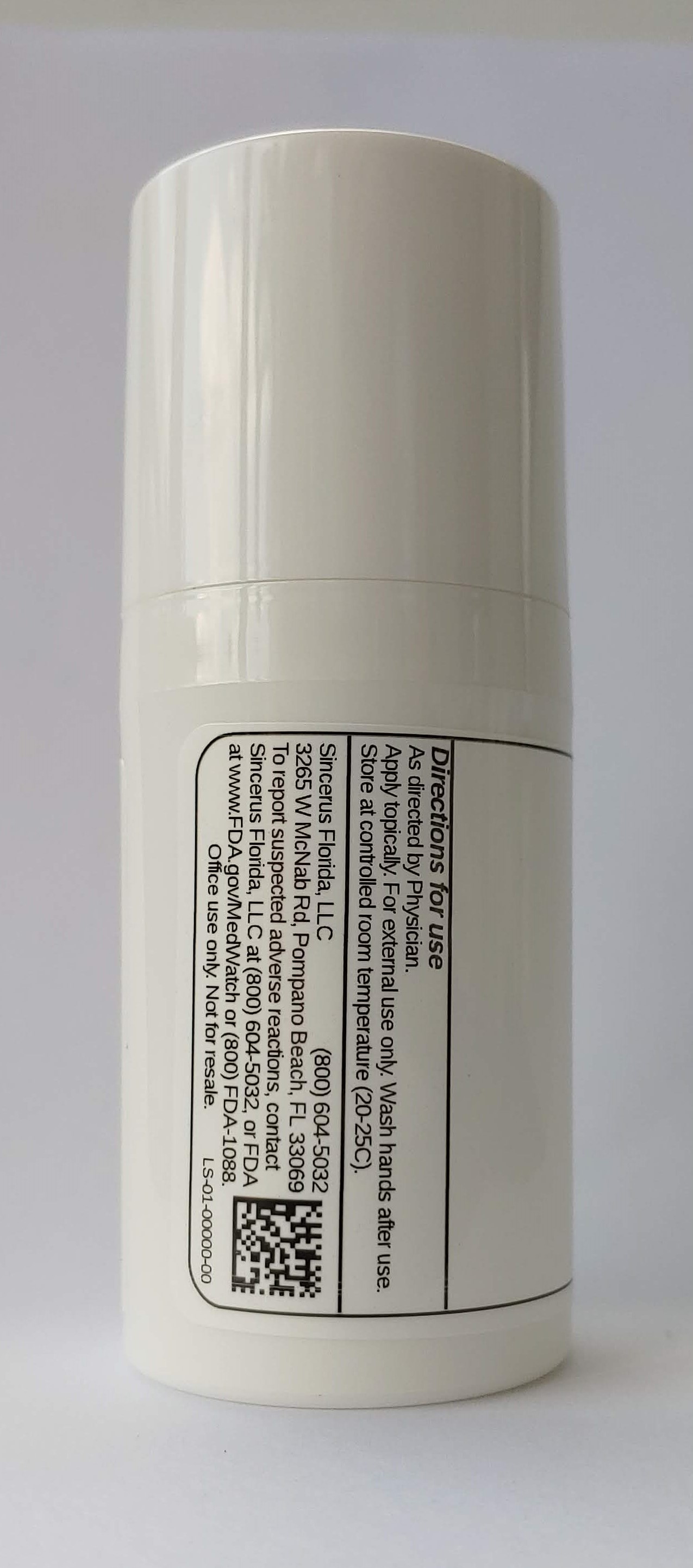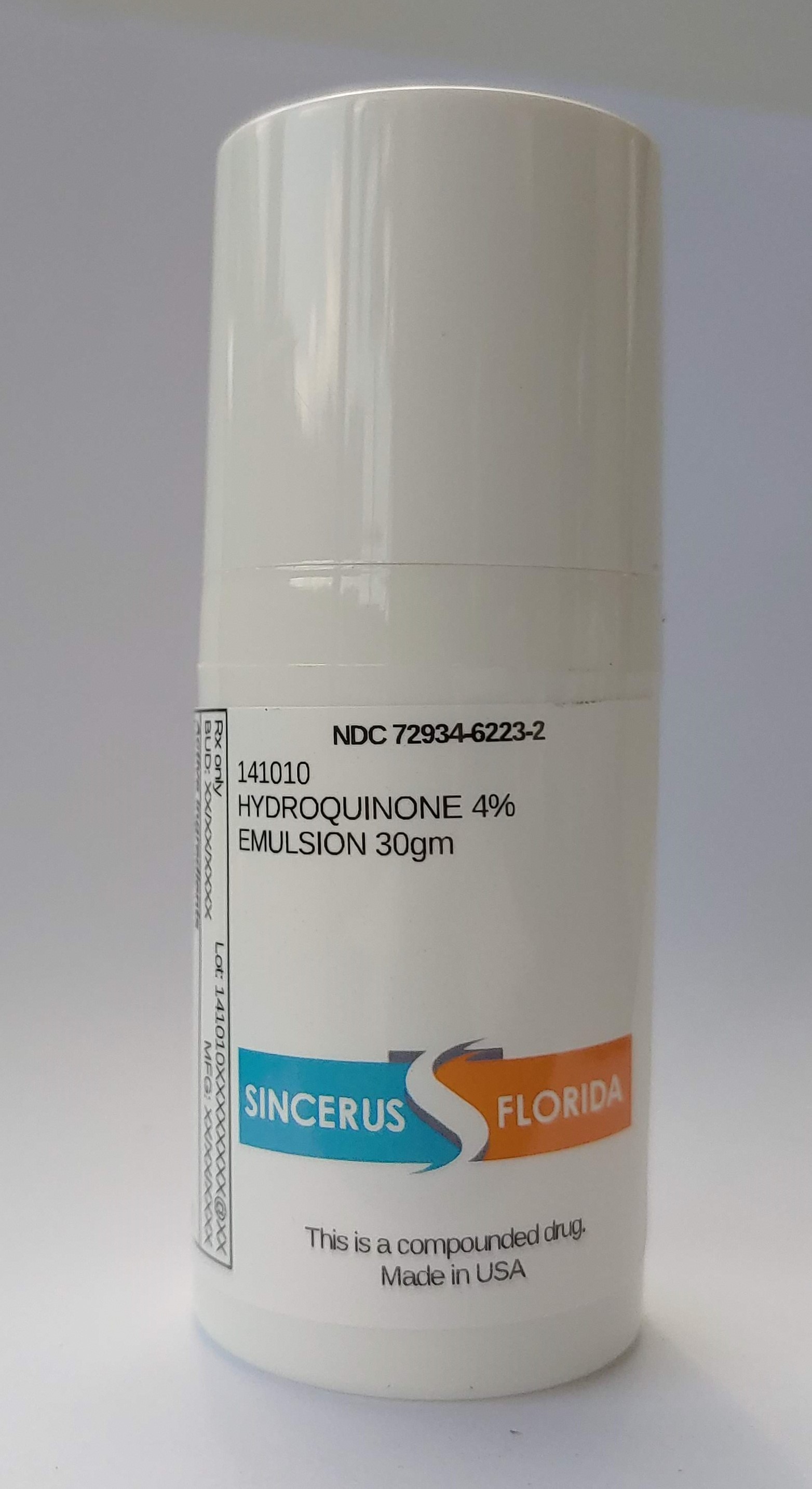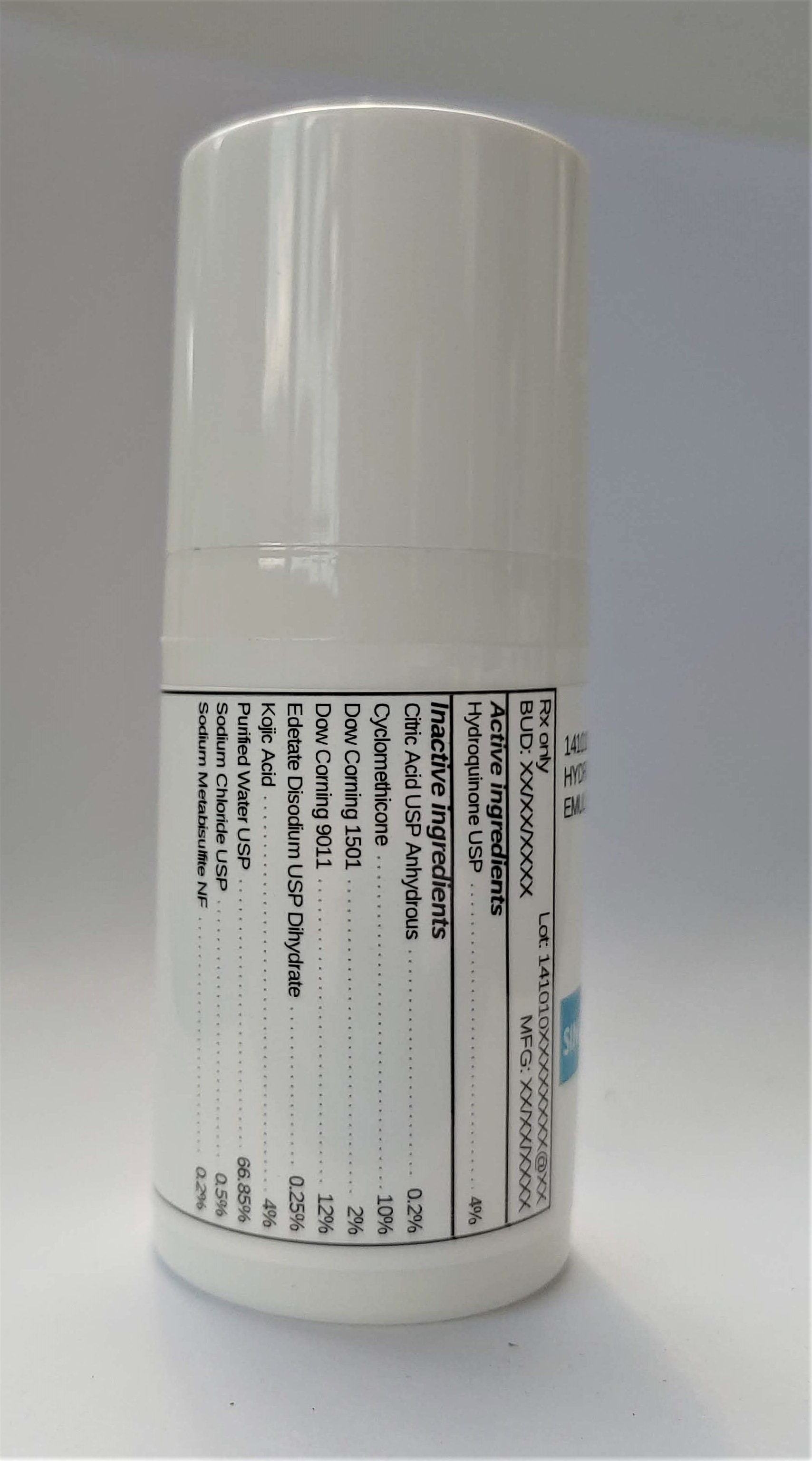 DRUG LABEL: 141010  HYDROQUINONE 4%
NDC: 72934-6223 | Form: EMULSION
Manufacturer: Sincerus Florida, LLC
Category: prescription | Type: HUMAN PRESCRIPTION DRUG LABEL
Date: 20200702

ACTIVE INGREDIENTS: HYDROQUINONE 4 g/100 g

141010 HYDROQUINONE 4%